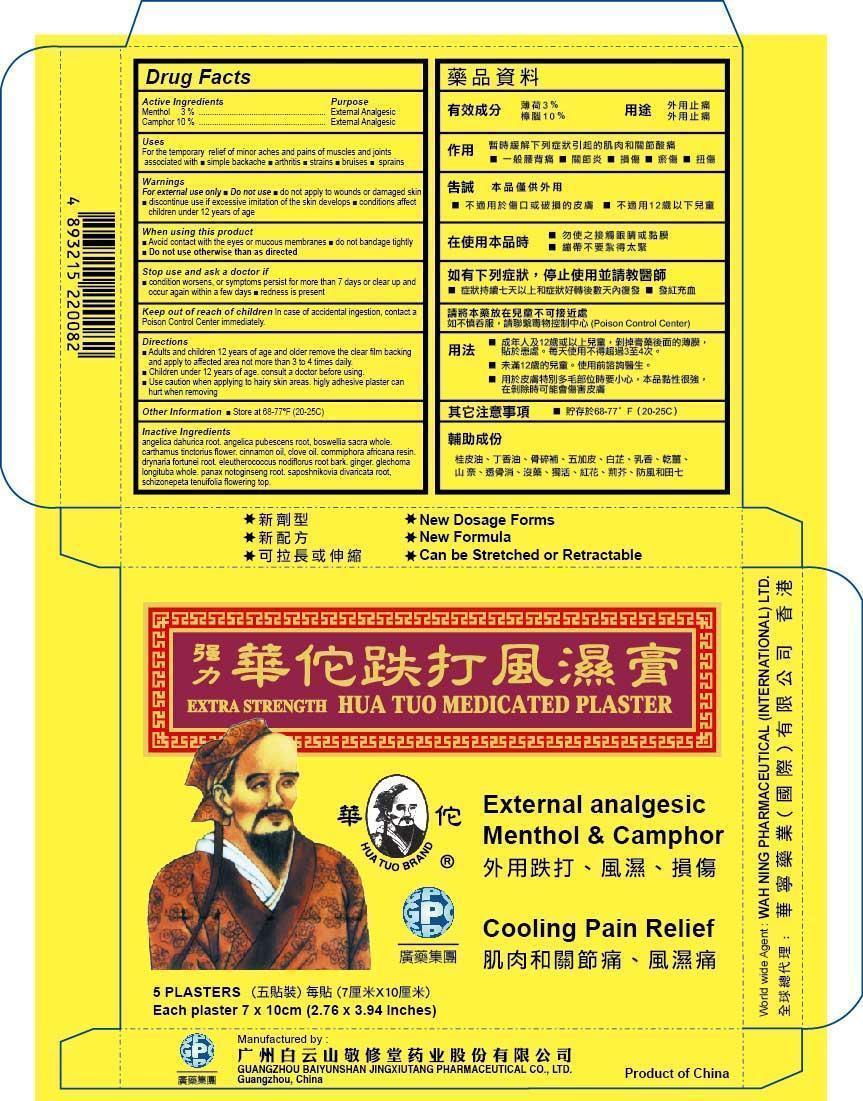 DRUG LABEL: Hua Tuo
NDC: 61821-100 | Form: PATCH
Manufacturer: GUANGZHOU BAIYUNSHAN JINGXIUTANG PHARMACEUTICAL COMPANY
Category: otc | Type: HUMAN OTC DRUG LABEL
Date: 20191031

ACTIVE INGREDIENTS: MENTHOL 3 g/1 1; CAMPHOR (SYNTHETIC) 10 g/1 1
INACTIVE INGREDIENTS: ANGELICA DAHURICA ROOT; ANGELICA PUBESCENS ROOT; BOSWELLIA SACRA WHOLE; CARTHAMUS TINCTORIUS FLOWER BUD; CINNAMON OIL; CLOVE OIL; COMMIPHORA AFRICANA RESIN; DRYNARIA FORTUNEI ROOT; ELEUTHEROCOCCUS NODIFLORUS ROOT BARK; GINGER; GLECHOMA LONGITUBA WHOLE; PANAX NOTOGINSENG ROOT; SAPOSHNIKOVIA DIVARICATA ROOT; NEPETA TENUIFOLIA FLOWERING TOP

Drug Facts

Active Ingredients

Menthol 3%
Camphor10%

Purpose

External Analgesic

External Analgesic

Uses

For the temporary relief of minor pains and aches of muscles and joints associated with ■ simple backache ■ arthritis ■ strains ■ bruises ■ sprains

Warnings

For external use only ■ Do not use ■ do not apply to wounds or damaged skin

■ discontinue use if excessive irritation of the skin develops ■ condition affect children uner 12 years of age

When using this product

■ Avoid contact with the eyes or mucus membranes ■ do not bandage tightly ■ Do not use otherwise than as directed

Stop use and ask a doctor if

■ condition worsens, or if symptoms persist for more than 7 days or clear up and occur again within a few days.

■ redness is present

Keep out of reach of children

In case of accidental ingestion, contact a doctor or Poison Control Center immediately

Directions

■ Adults and children 12 years of age and older remove the clear film backing

and apply to affected area not more than 3 to 4 times daily

■ Children under 12 years of age, consult a doctor before using.

■ Use caution when applying to hairy skin areas, highly adhesive plaster can hurt when removing.

Other Information

■ Store at 68-77ºF (20-25C)

Inactive Ingredients

angelica dahurica root, angelica pubescens root, boswellia sacra whole, carthamus tinctorius flower, cinnamon oil, clove oil, commiphora africana resin, drynaria fortunei root, eleutherococcus nodiflorus root bark, ginger, glechoma longituba whole, panax notoginseng root, saposhnikovia divaricata root, schizonepeta tenuifolia flowering top